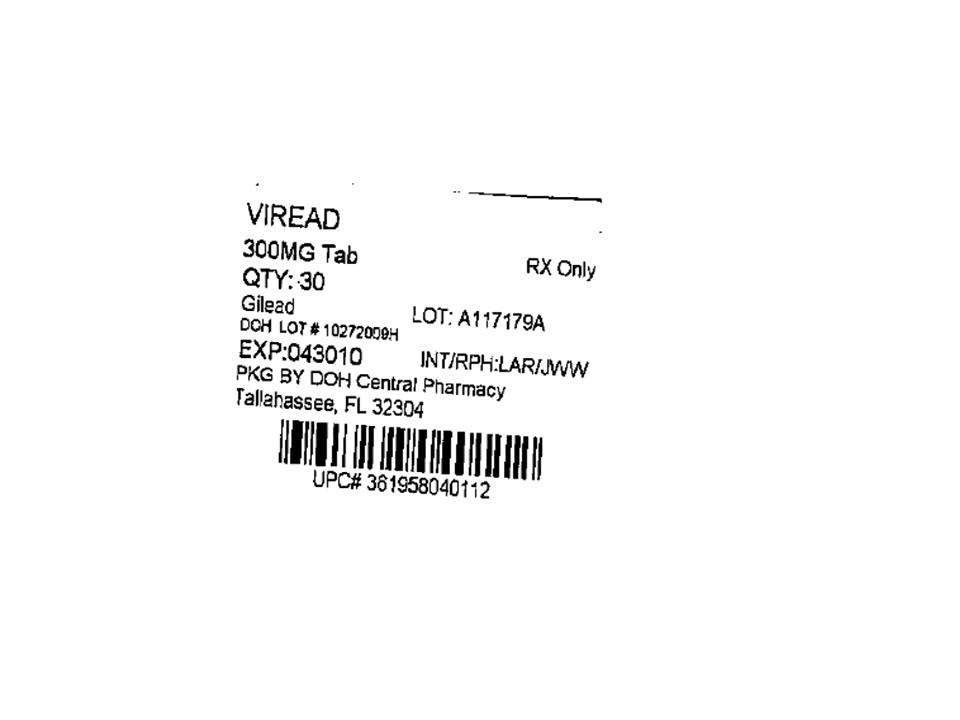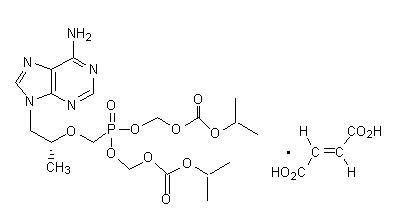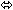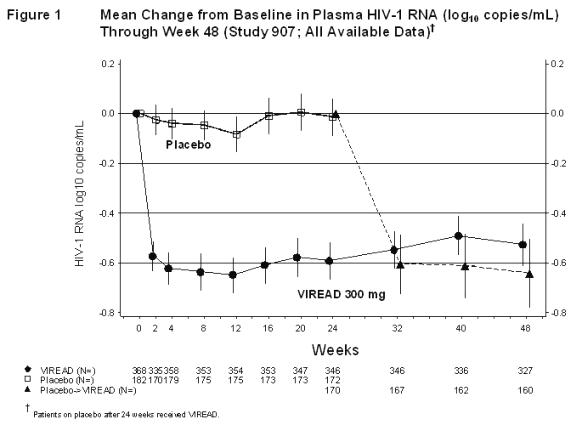 DRUG LABEL: Viread
NDC: 53808-0810 | Form: TABLET, COATED
Manufacturer: State of Florida DOH Central Pharmacy
Category: prescription | Type: HUMAN PRESCRIPTION DRUG LABEL
Date: 20100413

ACTIVE INGREDIENTS: TENOFOVIR DISOPROXIL FUMARATE 300 mg/1 1

HIGHLIGHTS OF PRESCRIBING INFORMATION

These highlights do not include all the information needed to use VIREAD safely and effectively. See full prescribing information for VIREAD.
VIREAD (tenofovir disoproxil fumarate) tablet, coated for oral use
Initial U.S. Approval: 2001

WARNINGS: LACTIC ACIDOSIS/SEVERE HEPATOMEGALY WITH STEATOSIS and POST TREATMENT EXACERBATION OF HEPATITIS

See full prescribing information for complete boxed warning.

- Lactic acidosis and severe hepatomegaly with steatosis, including fatal cases, have been reported with the use of nucleoside analogs, including VIREAD. (5.1)
- Severe acute exacerbations of hepatitis have been reported in HBV-infected patients who have discontinued anti-hepatitis B therapy, including VIREAD. Hepatic function should be monitored closely in these patients. If appropriate, resumption of anti-hepatitis B therapy may be warranted. (5.2)

RECENT MAJOR CHANGES

Boxed Warning | 8/2008, 11/2008
Indications and Usage (1.2) | 8/2008
Dosage and Administration (2.1) | 8/2008
Warnings and Precautions
Exacerbation of Hepatitis after Discontinuation of Treatment (5.2) | 8/2008
Decreases in Bone Mineral Density (5.6) | 11/2008
Early Virologic Failure (5.9) | 11/2008

1 INDICATIONS AND USAGE

VIREAD is a nucleotide analog HIV-1 reverse transcriptase and HBV polymerase inhibitor.

Viread is indicated in combination with other antiretroviral agents for the treatment of HIV-1 infection in adults. (1)

Viread is indicated for the treatment of chronic hepatitis B in adults. (1)

2 DOSAGE AND ADMINISTRATION

- Recommended dose for the treatment of HIV or chronic hepatitis B: 300 mg once daily taken orally without regard to food. (2.1)
- Dose recommended in renal impairment:
  Creatinine clearance 30–49 mL/min: 300 mg every 48 hours. (2.2)
  Creatinine clearance 10–29 mL/min: 300 mg every 72 to 96 hours. (2.2)
  Hemodialysis: 300 mg every 7 days or after approximately 12 hours of dialysis. (2.2)

3 DOSAGE FORMS AND STRENGTHS

Tablets: 300 mg. (3)

4 CONTRAINDICATIONS

None. (4)

5 WARNINGS AND PRECAUTIONS

- New onset or worsening renal impairment: Can include acute renal failure and Fanconi syndrome. Assess creatinine clearance (CrCl) before initiating treatment with VIREAD. Monitor CrCl and serum phosphorus in patients at risk. Avoid administering VIREAD with concurrent or recent use of nephrotoxic drugs, including HEPSERA. (5.3)
- Products with same active ingredient: Do not use with other tenofovir-containing products (e.g., ATRIPLA and TRUVADA). (5.4)
- HIV testing: HIV antibody testing should be offered to all HBV-infected patients before initiating therapy with VIREAD. VIREAD should only be used as part of an appropriate antiretroviral combination regimen in HIV-infected patients with or without HBV coinfection. (5.5)
- Decreases in bone mineral density (BMD): Observed in HIV-infected patients. Consider monitoring BMD in patients with a history of pathologic fracture or who are at risk for osteopenia. (5.6)
- Redistribution/accumulation of body fat: Observed in HIV-infected patients receiving antiretroviral combination therapy. (5.7)
- Immune reconstitution syndrome: Observed in HIV-infected patients. May necessitate further evaluation and treatment. (5.8)
- Triple nucleoside-only regimens: Early virologic failure has been reported in HIV-infected patients. Monitor carefully and consider treatment modification. (5.9)

6 ADVERSE REACTIONS

In HIV-infected patients: Most common adverse reactions (incidence ≥10%, Grades 2 – 4) are rash, diarrhea, headache, pain, depression, asthenia, and nausea. (6)

In HBV-infected patients: Most common adverse reaction (all grades) was nausea (9%). (6)

To report SUSPECTED ADVERSE REACTIONS, contact Gilead Sciences, Inc. at 1-800-GILEAD-5 or FDA at 1-800-FDA-1088 or www.fda.gov/medwatch

7 DRUG INTERACTIONS

- Didanosine: Coadministration increases didanosine concentrations. Use with caution and monitor for evidence of didanosine toxicity (e.g., pancreatitis, neuropathy). Consider dose reductions or discontinuations of didanosine if warranted. (7.1)
- Atazanavir: Coadministration decreases atazanavir concentrations and increases tenofovir concentrations. Use atazanavir with VIREAD only with additional ritonavir; monitor for evidence of tenofovir toxicity. (7.2)
- Lopinavir/ritonavir: Coadministration increases tenofovir concentrations. Monitor for evidence of tenofovir toxicity. (7.3)

8 USE IN SPECIFIC POPULATIONS

- Pregnancy: Pregnancy registry available. Enroll patients by calling 1-800-258-4263.
- Nursing mothers: Women infected with HIV should be instructed not to breast feed. (8.3)
- Safety and efficacy not established in patients less than 18 years of age. (8.4)

FULL PRESCRIBING INFORMATION

WARNINGS: LACTIC ACIDOSIS/SEVERE HEPATOMEGALY WITH STEATOSIS and POST TREATMENT EXACERBATION OF HEPATITIS

Lactic acidosis and severe hepatomegaly with steatosis, including fatal cases, have been reported with the use of nucleoside analogs, including VIREAD, in combination with other antiretrovirals [See Warnings and Precautions (5.1)].

Severe acute exacerbations of hepatitis have been reported in HBV-infected patients who have discontinued anti-hepatitis B therapy, including VIREAD. Hepatic function should be monitored closely with both clinical and laboratory follow-up for at least several months in patients who discontinue anti-hepatitis B therapy, including VIREAD. If appropriate, resumption of anti-hepatitis B therapy may be warranted [See Warnings and Precautions (5.2)].

1 INDICATIONS AND USAGE

1.1 HIV-1 Infection

VIREAD® is indicated in combination with other antiretroviral agents for the treatment of HIV-1 infection.

The following points should be considered when initiating therapy with VIREAD for the treatment of HIV-1 infection:

- VIREAD should not be used in combination with TRUVADA® or ATRIPLA® [See Warnings and Precautions (5.4)].

1.2 Chronic Hepatitis B

VIREAD is indicated for the treatment of chronic hepatitis B in adults.

The following points should be considered when initiating therapy with VIREAD for the treatment of HBV infection:

- This indication is based on data from one year of treatment in primarily nucleoside-treatment-naïve adult patients with HBeAg-positive and HBeAg-negative chronic hepatitis B with compensated liver disease [See Clinical Efficacy in Patients with Chronic Hepatitis B (14.2)].
- The numbers of patients in clinical trials who were nucleoside-experienced or who had lamivudine-associated mutations at baseline were too small to reach conclusions of efficacy [See Clinical Efficacy in Patients with Chronic Hepatitis B (14.2)].
- VIREAD has not been evaluated in patients with decompensated liver disease.

2 DOSAGE AND ADMINISTRATION

2.1 Recommended Dose

For the treatment of HIV-1 or chronic hepatitis B: The dose of VIREAD is 300 mg once daily taken orally, without regard to food.

In the treatment of chronic hepatitis B, the optimal duration of treatment is unknown.

2.2 Dose Adjustment for Renal Impairment

Significantly increased drug exposures occurred when VIREAD was administered to patients with moderate to severe renal impairment [See Clinical Pharmacology (12.3)]. Therefore, the dosing interval of VIREAD should be adjusted in patients with baseline creatinine clearance <50 mL/min using the recommendations in Table 1. These dosing interval recommendations are based on modeling of single-dose pharmacokinetic data in non-HIV and non-HBV infected subjects with varying degrees of renal impairment, including end-stage renal disease requiring hemodialysis. The safety and effectiveness of these dosing interval adjustment recommendations have not been clinically evaluated in patients with moderate or severe renal impairment, therefore clinical response to treatment and renal function should be closely monitored in these patients [See Warnings and Precautions (5.3)].

No dose adjustment is necessary for patients with mild renal impairment (creatinine clearance 50–80 mL/min). Routine monitoring of calculated creatinine clearance and serum phosphorus should be performed in patients with mild renal impairment [See Warnings and Precautions (5.3)].

Table 1 Dosage Adjustment for Patients with Altered Creatinine Clearance
 | Creatinine Clearance (mL/min) [Calculated using ideal (lean) body weight.]
 | ≥50 | 30–49 | 10–29 | Hemodialysis Patients
Recommended 300 mg Dosing Interval | Every 24 hours | Every 48 hours | Every 72 to 96 hours | Every 7 days or after a total of approximately 12 hours of dialysis [Generally once weekly assuming three hemodialysis sessions a week of approximately 4 hours duration. VIREAD should be administered following completion of dialysis.]

The pharmacokinetics of tenofovir have not been evaluated in non-hemodialysis patients with creatinine clearance <10 mL/min; therefore, no dosing recommendation is available for these patients.

3 DOSAGE FORMS AND STRENGTHS

VIREAD is available as tablets. Each tablet contains 300 mg of tenofovir disoproxil fumarate, which is equivalent to 245 mg of tenofovir disoproxil. The tablets are almond-shaped, light blue, film-coated, and debossed with "GILEAD" and "4331" on one side and with "300" on the other side.

4 CONTRAINDICATIONS

None.

5 WARNINGS AND PRECAUTIONS

5.1 Lactic Acidosis/Severe Hepatomegaly with Steatosis

Lactic acidosis and severe hepatomegaly with steatosis, including fatal cases, have been reported with the use of nucleoside analogs, including VIREAD, in combination with other antiretrovirals. A majority of these cases have been in women. Obesity and prolonged nucleoside exposure may be risk factors. Particular caution should be exercised when administering nucleoside analogs to any patient with known risk factors for liver disease; however, cases have also been reported in patients with no known risk factors. Treatment with VIREAD should be suspended in any patient who develops clinical or laboratory findings suggestive of lactic acidosis or pronounced hepatotoxicity (which may include hepatomegaly and steatosis even in the absence of marked transaminase elevations).

5.2 Exacerbation of Hepatitis after Discontinuation of Treatment

Discontinuation of anti-HBV therapy, including VIREAD, may be associated with severe acute exacerbations of hepatitis. Patients infected with HBV who discontinue VIREAD should be closely monitored with both clinical and laboratory follow-up for at least several months after stopping treatment. If appropriate, resumption of anti-hepatitis B therapy may be warranted.

5.3 New Onset or Worsening Renal Impairment

Tenofovir is principally eliminated by the kidney. Renal impairment, including cases of acute renal failure and Fanconi syndrome (renal tubular injury with severe hypophosphatemia), has been reported with the use of VIREAD [See Adverse Reactions (6.2)].

It is recommended that creatinine clearance be calculated in all patients prior to initiating therapy and as clinically appropriate during therapy with VIREAD. Routine monitoring of calculated creatinine clearance and serum phosphorus should be performed in patients at risk for renal impairment.

Dosing interval adjustment of VIREAD and close monitoring of renal function are recommended in all patients with creatinine clearance <50 mL/min [See Dosage and Administration (2.2)]. No safety or efficacy data are available in patients with renal impairment who received VIREAD using these dosing guidelines, so the potential benefit of VIREAD therapy should be assessed against the potential risk of renal toxicity.

VIREAD should be avoided with concurrent or recent use of a nephrotoxic agent.

5.4 Coadministration with Other Products

VIREAD should not be used in combination with the fixed-dose combination products TRUVADA or ATRIPLA since tenofovir disoproxil fumarate is a component of these products.

VIREAD should not be administered in combination with HEPSERA® (adefovir dipivoxil) [See Drug Interactions (7.4)].

5.5 Patients Coinfected with HIV-1 and HBV

Due to the risk of development of HIV-1 resistance, VIREAD should only be used in HIV-1 and HBV coinfected patients as part of an appropriate antiretroviral combination regimen.

HIV-1 antibody testing should be offered to all HBV-infected patients before initiating therapy with VIREAD. It is also recommended that all patients with HIV-1 be tested for the presence of chronic hepatitis B before initiating treatment with VIREAD.

5.6 Decreases in Bone Mineral Density

Bone mineral density (BMD) monitoring should be considered for patients who have a history of pathologic bone fracture or are at risk for osteopenia. Although the effect of supplementation with calcium and vitamin D was not studied, such supplementation may be beneficial for all patients. If bone abnormalities are suspected then appropriate consultation should be obtained.

In HIV-infected patients treated with VIREAD in Study 903 through 144 weeks, decreases from baseline in BMD were seen at the lumbar spine and hip in both arms of the study. At Week 144, there was a significantly greater mean percentage decrease from baseline in BMD at the lumbar spine in patients receiving VIREAD + lamivudine + efavirenz (-2.2% ± 3.9) compared with patients receiving stavudine + lamivudine + efavirenz (-1.0% ± 4.6). Changes in BMD at the hip were similar between the two treatment groups (-2.8% ± 3.5 in the VIREAD group vs. -2.4% ± 4.5 in the stavudine group). In both groups, the majority of the reduction in BMD occurred in the first 24–48 weeks of the study and this reduction was sustained through Week 144. Twenty-eight percent of VIREAD-treated patients vs. 21% of the stavudine-treated patients lost at least 5% of BMD at the spine or 7% of BMD at the hip. Clinically relevant fractures (excluding fingers and toes) were reported in 4 patients in the VIREAD group and 6 patients in the stavudine group. In addition, there were significant increases in biochemical markers of bone metabolism (serum bone-specific alkaline phosphatase, serum osteocalcin, serum C-telopeptide, and urinary N-telopeptide) in the VIREAD group relative to the stavudine group, suggesting increased bone turnover. Serum parathyroid hormone levels and 1,25 Vitamin D levels were also higher in the VIREAD group. Except for bone specific alkaline phosphatase, these changes resulted in values that remained within the normal range. The effects of VIREAD-associated changes in BMD and biochemical markers on long-term bone health and future fracture risk are unknown.

Cases of osteomalacia (associated with proximal renal tubulopathy and which may contribute to fractures) have been reported in association with the use of VIREAD [See Adverse Reactions (6.2)].

The bone effects of VIREAD have not been studied in patients with chronic HBV infection.

5.7 Fat Redistribution

In HIV-infected patients redistribution/accumulation of body fat including central obesity, dorsocervical fat enlargement (buffalo hump), peripheral wasting, facial wasting, breast enlargement, and "cushingoid appearance" have been observed in patients receiving combination antiretroviral therapy. The mechanism and long-term consequences of these events are currently unknown. A causal relationship has not been established.

5.8 Immune Reconstitution Syndrome

Immune reconstitution syndrome has been reported in HIV-infected patients treated with combination antiretroviral therapy, including VIREAD. During the initial phase of combination antiretroviral treatment, patients whose immune system responds may develop an inflammatory response to indolent or residual opportunistic infections [such as Mycobacterium avium infection, cytomegalovirus, Pneumocystis jirovecii pneumonia (PCP), or tuberculosis], which may necessitate further evaluation and treatment.

5.9 Early Virologic Failure

Clinical studies in HIV-infected patients have demonstrated that certain regimens that only contain three nucleoside reverse transcriptase inhibitors (NRTI) are generally less effective than triple drug regimens containing two NRTIs in combination with either a non-nucleoside reverse transcriptase inhibitor or a HIV-1 protease inhibitor. In particular, early virological failure and high rates of resistance substitutions have been reported. Triple nucleoside regimens should therefore be used with caution. Patients on a therapy utilizing a triple nucleoside-only regimen should be carefully monitored and considered for treatment modification.

6 ADVERSE REACTIONS

The following adverse reactions are discussed in other sections of the labeling:

- Lactic Acidosis/Severe Hepatomegaly with Steatosis [See Boxed Warning, Warnings and Precautions (5.1)].
- Severe Acute Exacerbation of Hepatitis [See Boxed Warning, Warnings and Precautions (5.2)].
- New Onset or Worsening Renal Impairment [See Warnings and Precautions (5.3)].
- Decreases in Bone Mineral Density [See Warnings and Precautions (5.6)].
- Immune Reconstitution Syndrome [See Warnings and Precautions (5.8)].

6.1 Adverse Reactions from Clinical Trials Experience

Because clinical trials are conducted under widely varying conditions, adverse reaction rates observed in the clinical trials of a drug cannot be directly compared to rates in the clinical trials of another drug and may not reflect the rates observed in practice.

Clinical Trials in Patients with HIV Infection

More than 12,000 patients have been treated with VIREAD alone or in combination with other antiretroviral medicinal products for periods of 28 days to 215 weeks in clinical trials and expanded access studies. A total of 1,544 patients have received VIREAD 300 mg once daily in clinical trials; over 11,000 patients have received VIREAD in expanded access studies.

The most common adverse reactions (incidence ≥10%, Grades 2–4) identified from any of the 3 large controlled clinical trials include rash, diarrhea, headache, pain, depression, asthenia, and nausea.

Treatment-Naïve Patients

Study 903 - Treatment-Emergent Adverse Reactions: The most common adverse reactions seen in a double-blind comparative controlled study in which 600 treatment-naïve patients received VIREAD (N=299) or stavudine (N=301) in combination with lamivudine and efavirenz for 144 weeks (Study 903) were mild to moderate gastrointestinal events and dizziness.

Mild adverse reactions (Grade 1) were common with a similar incidence in both arms, and included dizziness, diarrhea, and nausea. Selected treatment-emergent moderate to severe adverse reactions are summarized in Table 2.

Table 2 Selected Treatment-Emergent Adverse Reactions [Frequencies of adverse reactions are based on all treatment-emergent adverse events, regardless of relationship to study drug.] (Grades 2–4) Reported in ≥5% in Any Treatment Group in Study 903 (0–144 Weeks)
 | VIREAD + 3TC + EFV | d4T + 3TC + EFV
 | N=299 | N=301
Body as a Whole
Headache | 14% | 17%
Pain | 13% | 12%
Fever | 8% | 7%
Abdominal pain | 7% | 12%
Back pain | 9% | 8%
Asthenia | 6% | 7%
Digestive System
Diarrhea | 11% | 13%
Nausea | 8% | 9%
Dyspepsia | 4% | 5%
Vomiting | 5% | 9%
Metabolic Disorders
Lipodystrophy [Lipodystrophy represents a variety of investigator-described adverse events not a protocol-defined syndrome.] | 1% | 8%
Musculoskeletal
Arthralgia | 5% | 7%
Myalgia | 3% | 5%
Nervous System
Depression | 11% | 10%
Insomnia | 5% | 8%
Dizziness | 3% | 6%
Peripheral neuropathy [Peripheral neuropathy includes peripheral neuritis and neuropathy.] | 1% | 5%
Anxiety | 6% | 6%
Respiratory
Pneumonia | 5% | 5%
Skin and Appendages
Rash event [Rash event includes rash, pruritus, maculopapular rash, urticaria, vesiculobullous rash, and pustular rash.] | 18% | 12%

Laboratory Abnormalities: With the exception of fasting cholesterol and fasting triglyceride elevations that were more common in the stavudine group (40% and 9%) compared with VIREAD (19% and 1%) respectively, laboratory abnormalities observed in this study occurred with similar frequency in the VIREAD and stavudine treatment arms. A summary of Grade 3 and 4 laboratory abnormalities is provided in Table 3.

Table 3 Grade 3/4 Laboratory Abnormalities Reported in ≥1% of VIREAD-Treated Patients in Study 903 (0–144 Weeks)
 | VIREAD + 3TC + EFV | d4T + 3TC + EFV
 | N=299 | N=301
Any ≥ Grade 3 Laboratory Abnormality | 36% | 42%
Fasting Cholesterol (>240 mg/dL) | 19% | 40%
Creatine Kinase (M: >990 U/L) (F: >845 U/L) | 12% | 12%
Serum Amylase (>175 U/L) | 9% | 8%
AST (M: >180 U/L) (F: >170 U/L) | 5% | 7%
ALT (M: >215 U/L) (F: >170 U/L) | 4% | 5%
Hematuria (>100 RBC/HPF) | 7% | 7%
Neutrophils (<750/mm^3) | 3% | 1%
Fasting Triglycerides (>750 mg/dL) | 1% | 9%

Study 934 - Treatment Emergent Adverse Reactions: In Study 934, 511 antiretroviral-naïve patients received either VIREAD + EMTRIVA® administered in combination with efavirenz (N=257) or zidovudine/lamivudine administered in combination with efavirenz (N=254). Adverse reactions observed in this study were generally consistent with those seen in previous studies in treatment-experienced or treatment-naïve patients (Table 4).

Table 4 Selected Treatment-Emergent Adverse Reactions [Frequencies of adverse reactions are based on all treatment-emergent adverse events, regardless of relationship to study drug.] (Grades 2–4) Reported in ≥5% in Any Treatment Group in Study 934 (0–144 Weeks)
 | VIREAD [From Weeks 96 to 144 of the study, patients received TRUVADA with efavirenz in place of VIREAD + EMTRIVA with efavirenz.] + FTC + EFV | AZT/3TC + EFV
 | N=257 | N=254
Gastrointestinal Disorder
Diarrhea | 9% | 5%
Nausea | 9% | 7%
Vomiting | 2% | 5%
General Disorders and Administration Site Condition
Fatigue | 9% | 8%
Infections and Infestations
Sinusitis | 8% | 4%
Upper respiratory tract infections | 8% | 5%
Nasopharyngitis | 5% | 3%
Nervous System Disorders
Headache | 6% | 5%
Dizziness | 8% | 7%
Psychiatric Disorders
Depression | 9% | 7%
Insomnia | 5% | 7%
Skin and Subcutaneous Tissue Disorders
Rash event [Rash event includes rash, exfoliative rash, rash generalized, rash macular, rash maculo-papular, rash pruritic, and rash vesicular.] | 7% | 9%

Laboratory Abnormalities: Laboratory abnormalities observed in this study were generally consistent with those seen in previous studies (Table 5).

Table 5 Significant Laboratory Abnormalities Reported in ≥1% of Patients in Any Treatment Group in Study 934 (0–144 Weeks)
 | VIREAD [From Weeks 96 to 144 of the study, patients received TRUVADA with efavirenz in place of VIREAD + EMTRIVA with efavirenz.] + FTC + EFV | AZT/3TC + EFV
 | N=257 | N=254
Any ≥ Grade 3 Laboratory Abnormality | 30% | 26%
Fasting Cholesterol (>240 mg/dL) | 22% | 24%
Creatine Kinase (M: >990 U/L) (F: >845 U/L) | 9% | 7%
Serum Amylase (>175 U/L) | 8% | 4%
Alkaline Phosphatase (>550 U/L) | 1% | 0%
AST (M: >180 U/L) (F: >170 U/L) | 3% | 3%
ALT (M: >215 U/L) (F: >170 U/L) | 2% | 3%
Hemoglobin (<8.0 mg/dL) | 0% | 4%
Hyperglycemia (>250 mg/dL) | 2% | 1%
Hematuria (>75 RBC/HPF) | 3% | 2%
Glycosuria (≥3+) | <1% | 1%
Neutrophils (<750/mm^3) | 3% | 5%
Fasting Triglycerides (>750 mg/dL) | 4% | 2%

Treatment-Experienced Patients

Treatment-Emergent Adverse Reactions: The adverse reactions seen in treatment experienced patients were generally consistent with those seen in treatment naïve patients including mild to moderate gastrointestinal events, such as nausea, diarrhea, vomiting, and flatulence. Less than 1% of patients discontinued participation in the clinical studies due to gastrointestinal adverse reactions (Study 907).

A summary of moderate to severe, treatment-emergent adverse reactions that occurred during the first 48 weeks of Study 907 is provided in Table 6.

Table 6 Selected Treatment-Emergent Adverse Reactions [Frequencies of adverse reactions are based on all treatment-emergent adverse events, regardless of relationship to study drug.] (Grades 2–4) Reported in ≥3% in Any Treatment Group in Study 907 (0–48 Weeks)
 | VIREAD (N=368) (Week 0–24) | Placebo (N=182) (Week 0–24) | VIREAD (N=368) (Week 0–48) | Placebo Crossover to VIREAD (N=170) (Week 24–48)
Body as a Whole
Asthenia | 7% | 6% | 11% | 1%
Pain | 7% | 7% | 12% | 4%
Headache | 5% | 5% | 8% | 2%
Abdominal pain | 4% | 3% | 7% | 6%
Back pain | 3% | 3% | 4% | 2%
Chest pain | 3% | 1% | 3% | 2%
Fever | 2% | 2% | 4% | 2%
Digestive System
Diarrhea | 11% | 10% | 16% | 11%
Nausea | 8% | 5% | 11% | 7%
Vomiting | 4% | 1% | 7% | 5%
Anorexia | 3% | 2% | 4% | 1%
Dyspepsia | 3% | 2% | 4% | 2%
Flatulence | 3% | 1% | 4% | 1%
Respiratory
Pneumonia | 2% | 0% | 3% | 2%
Nervous System
Depression | 4% | 3% | 8% | 4%
Insomnia | 3% | 2% | 4% | 4%
Peripheral neuropathy [Peripheral neuropathy includes peripheral neuritis and neuropathy.] | 3% | 3% | 5% | 2%
Dizziness | 1% | 3% | 3% | 1%
Skin and Appendage
Rash event [Rash event includes rash, pruritus, maculopapular rash, urticaria, vesiculobullous rash, and pustular rash.] | 5% | 4% | 7% | 1%
Sweating | 3% | 2% | 3% | 1%
Musculoskeletal
Myalgia | 3% | 3% | 4% | 1%
Metabolic
Weight loss | 2% | 1% | 4% | 2%

Laboratory Abnormalities: Laboratory abnormalities observed in this study occurred with similar frequency in the VIREAD and placebo-treated groups. A summary of Grade 3 and 4 laboratory abnormalities is provided in Table 7.

Table 7 Grade 3/4 Laboratory Abnormalities Reported in ≥1% of VIREAD-Treated Patients in Study 907 (0–48 Weeks)
 | VIREAD (N=368) (Week 0–24) | Placebo (N=182) (Week 0–24) | VIREAD (N=368) (Week 0–48) | Placebo Crossover to VIREAD (N=170) (Week 24–48)
Any ≥ Grade 3 Laboratory Abnormality | 25% | 38% | 35% | 34%
Triglycerides (>750 mg/dL) | 8% | 13% | 11% | 9%
Creatine Kinase (M: >990U/L) (F: >845 U/L) | 7% | 14% | 12% | 12%
Serum Amylase (>175 U/L) | 6% | 7% | 7% | 6%
Glycosuria (≥3+) | 3% | 3% | 3% | 2%
AST (M: >180 U/L) (F: >170 U/L) | 3% | 3% | 4% | 5%
ALT (M: >215 U/L) (F: >170 U/L) | 2% | 2% | 4% | 5%
Serum Glucose (>250 U/L) | 2% | 4% | 3% | 3%
Neutrophils (<750/mm^3) | 1% | 1% | 2% | 1%

Clinical Trials in Patients with Chronic Hepatitis B

Treatment-Emergent Adverse Reactions: In controlled clinical trials in patients with chronic hepatitis B, more patients treated with VIREAD experienced nausea: 9% with VIREAD versus 2% with HEPSERA. Other treatment-emergent adverse reactions reported in >5% of patients treated with VIREAD included: abdominal pain, diarrhea, headache, dizziness, fatigue, nasopharyngitis, back pain and skin rash.

Laboratory Abnormalities: A summary of Grade 3 and 4 laboratory abnormalities is provided in Table 8.

Table 8. Grade 3/4 Laboratory Abnormalities Reported in ≥1% of VIREAD-Treated Patients in Studies 0102 and 0103 (0-48 Weeks)
 | VIREAD (N=426) | HEPSERA (N=215)
Any ≥ Grade 3 Laboratory Abnormality | 19% | 13%
Creatine Kinase (M: >990U/L) (F: >845 U/L) | 2% | 3%
Serum Amylase (>175 U/L) | 4% | 1%
Glycosuria (≥3+) | 3% | <1%
AST (M: >180 U/L) (F: >170 U/L) | 4% | 4%
ALT (M: >215 U/L) (F: >170 U/L) | 10% | 6%

The overall incidence of on-treatment ALT elevations (defined as serum ALT >2 × baseline and >10 × ULN, with or without associated symptoms) was similar between VIREAD (2.6%) and HEPSERA (2%). ALT elevations generally occurred within the first 4–8 weeks of treatment and were accompanied by decreases in HBV DNA levels. No patient had evidence of decompensation. ALT flares typically resolved within 4 to 8 weeks without changes in study medication.

6.2 Postmarketing Experience

The following adverse reactions have been identified during postapproval use of VIREAD. Because postmarketing reactions are reported voluntarily from a population of uncertain size, it is not always possible to reliably estimate their frequency or establish a causal relationship to drug exposure.

Immune System Disorders
allergic reaction

Metabolism and Nutrition Disorders
lactic acidosis, hypokalemia, hypophosphatemia

Respiratory, Thoracic, and Mediastinal Disorders
dyspnea

Gastrointestinal Disorders
pancreatitis, increased amylase, abdominal pain

Hepatobiliary Disorders
hepatic steatosis, hepatitis, increased liver enzymes (most commonly AST, ALT gamma GT)

Skin and Subcutaneous Tissue Disorders
rash

Musculoskeletal and Connective Tissue Disorders
rhabdomyolysis, osteomalacia (manifested as bone pain and which may contribute to fractures), muscular weakness, myopathy

Renal and Urinary Disorders
acute renal failure, renal failure, acute tubular necrosis, Fanconi syndrome, proximal renal tubulopathy, interstitial nephritis (including acute cases), nephrogenic diabetes insipidus, renal insufficiency, increased creatinine, proteinuria, polyuria

General Disorders and Administration Site Conditions
asthenia

The following adverse reactions, listed under the body system headings above, may occur as a consequence of proximal renal tubulopathy: rhabdomyolysis, osteomalacia, hypokalemia, muscular weakness, myopathy, hypophosphatemia.

7 DRUG INTERACTIONS

This section describes clinically relevant drug interactions with VIREAD. Drug interactions studies are described elsewhere in the labeling [See Clinical Pharmacology (12.3)].

7.1 Didanosine

Coadministration of VIREAD and didanosine should be undertaken with caution and patients receiving this combination should be monitored closely for didanosine-associated adverse reactions. Didanosine should be discontinued in patients who develop didanosine-associated adverse reactions.

When administered with VIREAD, Cmax and AUC of didanosine (administered as either the buffered or enteric-coated formulation) increased significantly [See Clinical Pharmacology (12.3)]. The mechanism of this interaction is unknown. Higher didanosine concentrations could potentiate didanosine-associated adverse reactions, including pancreatitis and neuropathy. Suppression of CD4^+ cell counts has been observed in patients receiving tenofovir disoproxil fumarate (tenofovir DF) with didanosine 400 mg daily.

In adults weighing >60 kg, the didanosine dose should be reduced to 250 mg when it is coadministered with VIREAD. Data are not available to recommend a dose adjustment of didanosine for patients weighing <60 kg. When coadministered, VIREAD and didanosine EC may be taken under fasted conditions or with a light meal (<400 kcal, 20% fat). Coadministration of didanosine buffered tablet formulation with VIREAD should be under fasted conditions.

7.2 Atazanavir

Atazanavir has been shown to increase tenofovir concentrations [See Clinical Pharmacology (12.3)]. The mechanism of this interaction is unknown. Patients receiving atazanavir and VIREAD should be monitored for VIREAD-associated adverse reactions. VIREAD should be discontinued in patients who develop VIREAD-associated adverse reactions.

VIREAD decreases the AUC and Cmin of atazanavir [See Clinical Pharmacology (12.3)]. When coadministered with VIREAD, it is recommended that atazanavir 300 mg is given with ritonavir 100 mg. Atazanavir without ritonavir should not be coadministered with VIREAD.

7.3 Lopinavir/Ritonavir

Lopinavir/ritonavir has been shown to increase tenofovir concentrations [See Clinical Pharmacology (12.3)]. The mechanism of this interaction is unknown. Patients receiving lopinavir/ritonavir and VIREAD should be monitored for VIREAD-associated adverse reactions. VIREAD should be discontinued in patients who develop VIREAD-associated adverse reactions.

7.4 Drugs Affecting Renal Function

Since tenofovir is primarily eliminated by the kidneys [See Clinical Pharmacology (12.3)], coadministration of VIREAD with drugs that reduce renal function or compete for active tubular secretion may increase serum concentrations of tenofovir and/or increase the concentrations of other renally eliminated drugs. Some examples include, but are not limited to cidofovir, acyclovir, valacyclovir, ganciclovir, and valganciclovir. Drugs that decrease renal function may also increase serum concentrations of tenofovir.

In the treatment of chronic hepatitis B, VIREAD should not be administered in combination with HEPSERA (adefovir dipivoxil).

8 USE IN SPECIFIC POPULATIONS

TERATOGENIC EFFECTS

Pregnancy Category B

Reproduction studies have been performed in rats and rabbits at doses up to 14 and 19 times the human dose based on body surface area comparisons and revealed no evidence of impaired fertility or harm to the fetus due to tenofovir. There are, however, no adequate and well-controlled studies in pregnant women. Because animal reproduction studies are not always predictive of human response, VIREAD should be used during pregnancy only if clearly needed.

Antiretroviral Pregnancy Registry: To monitor fetal outcomes of pregnant women exposed to VIREAD, an Antiretroviral Pregnancy Registry has been established. Healthcare providers are encouraged to register patients by calling 1-800-258-4263.

8.3 Nursing Mothers

Nursing Mothers: The Centers for Disease Control and Prevention recommend that HIV-1-infected mothers not breast-feed their infants to avoid risking postnatal transmission of HIV-1. Studies in rats have demonstrated that tenofovir is secreted in milk. It is not known whether tenofovir is excreted in human milk. Because of both the potential for HIV-1 transmission and the potential for serious adverse reactions in nursing infants, mothers should be instructed not to breast-feed if they are receiving VIREAD.

8.4 Pediatric Use

Safety and effectiveness in patients less than 18 years of age have not been established.

8.5 Geriatric Use

Clinical studies of VIREAD did not include sufficient numbers of subjects aged 65 and over to determine whether they respond differently from younger subjects. In general, dose selection for the elderly patient should be cautious, keeping in mind the greater frequency of decreased hepatic, renal, or cardiac function, and of concomitant disease or other drug therapy.

8.6 Patients with Impaired Renal Function

It is recommended that the dosing interval for VIREAD be modified in patients with creatinine clearance <50 mL/min or in patients with ESRD who require dialysis [See Dosage and Administration (2.2), Clinical Pharmacology (12.3)].

10 OVERDOSAGE

Limited clinical experience at doses higher than the therapeutic dose of VIREAD 300 mg is available. In Study 901, 600 mg tenofovir disoproxil fumarate was administered to 8 patients orally for 28 days. No severe adverse reactions were reported. The effects of higher doses are not known.

If overdose occurs the patient must be monitored for evidence of toxicity, and standard supportive treatment applied as necessary.

Tenofovir is efficiently removed by hemodialysis with an extraction coefficient of approximately 54%. Following a single 300 mg dose of VIREAD, a four-hour hemodialysis session removed approximately 10% of the administered tenofovir dose.

11 DESCRIPTION

VIREAD is the brand name for tenofovir disoproxil fumarate (a prodrug of tenofovir) which is a fumaric acid salt of bis-isopropoxycarbonyloxymethyl ester derivative of tenofovir. In vivo tenofovir disoproxil fumarate is converted to tenofovir, an acyclic nucleoside phosphonate (nucleotide) analog of adenosine 5'-monophosphate. Tenofovir exhibits activity against HIV-1 reverse transcriptase.

The chemical name of tenofovir disoproxil fumarate is 9-[(R)-2-[[bis[[(isopropoxycarbonyl)oxy]methoxy]phosphinyl]methoxy]propyl]adenine fumarate (1:1). It has a molecular formula of C19H30N5O10P • C4H4O4 and a molecular weight of 635.52. It has the following structural formula:

Tenofovir disoproxil fumarate is a white to off-white crystalline powder with a solubility of 13.4 mg/mL in distilled water at 25 °C. It has an octanol/phosphate buffer (pH 6.5) partition coefficient (log p) of 1.25 at 25 °C.

VIREAD tablets are for oral administration. Each tablet contains 300 mg of tenofovir disoproxil fumarate, which is equivalent to 245 mg of tenofovir disoproxil, and the following inactive ingredients: croscarmellose sodium, lactose monohydrate, magnesium stearate, microcrystalline cellulose, and pregelatinized starch. The tablets are coated with Opadry II Y–30–10671–A, which contains FD&C blue #2 aluminum lake, hydroxypropyl methylcellulose 2910, lactose monohydrate, titanium dioxide, and triacetin.

In this insert, all dosages are expressed in terms of tenofovir disoproxil fumarate except where otherwise noted.

12 CLINICAL PHARMACOLOGY

12.1 Mechanism of Action

Tenofovir disoproxil fumarate is an antiviral drug [See Clinical Pharmacology (12.4)].

12.3 Pharmacokinetics

The pharmacokinetics of tenofovir disoproxil fumarate have been evaluated in healthy volunteers and HIV-1 infected individuals. Tenofovir pharmacokinetics are similar between these populations.

Absorption

VIREAD is a water soluble diester prodrug of the active ingredient tenofovir. The oral bioavailability of tenofovir from VIREAD in fasted patients is approximately 25%. Following oral administration of a single dose of VIREAD 300 mg to HIV-1 infected patients in the fasted state, maximum serum concentrations (Cmax) are achieved in 1.0 ± 0.4 hrs. Cmax and AUC values are 0.30 ± 0.09 µg/mL and 2.29 ± 0.69 µg∙hr/mL, respectively.

The pharmacokinetics of tenofovir are dose proportional over a VIREAD dose range of 75 to 600 mg and are not affected by repeated dosing.

Distribution

In vitro binding of tenofovir to human plasma or serum proteins is less than 0.7 and 7.2%, respectively, over the tenofovir concentration range 0.01 to 25 µg/mL. The volume of distribution at steady-state is 1.3 ± 0.6 L/kg and 1.2 ± 0.4 L/kg, following intravenous administration of tenofovir 1.0 mg/kg and 3.0 mg/kg.

Metabolism and Elimination

In vitro studies indicate that neither tenofovir disoproxil nor tenofovir are substrates of CYP enzymes.

Following IV administration of tenofovir, approximately 70–80% of the dose is recovered in the urine as unchanged tenofovir within 72 hours of dosing. Following single dose, oral administration of VIREAD, the terminal elimination half-life of tenofovir is approximately 17 hours. After multiple oral doses of VIREAD 300 mg once daily (under fed conditions), 32 ± 10% of the administered dose is recovered in urine over 24 hours.

Tenofovir is eliminated by a combination of glomerular filtration and active tubular secretion. There may be competition for elimination with other compounds that are also renally eliminated.

Effects of Food on Oral Absorption

Administration of VIREAD following a high-fat meal (~700 to 1000 kcal containing 40 to 50% fat) increases the oral bioavailability, with an increase in tenofovir AUC0–∞ of approximately 40% and an increase in Cmax of approximately 14%. However, administration of VIREAD with a light meal did not have a significant effect on the pharmacokinetics of tenofovir when compared to fasted administration of the drug. Food delays the time to tenofovir Cmax by approximately 1 hour. Cmax and AUC of tenofovir are 0.33 ± 0.12 µg/mL and 3.32 ± 1.37 µg∙hr/mL following multiple doses of VIREAD 300 mg once daily in the fed state, when meal content was not controlled.

Special Populations

Race: There were insufficient numbers from racial and ethnic groups other than Caucasian to adequately determine potential pharmacokinetic differences among these populations.

Gender: Tenofovir pharmacokinetics are similar in male and female patients.

Pediatric and Geriatric Patients: Pharmacokinetic studies have not been performed in children (<18 years) or in the elderly (>65 years).

Patients with Impaired Renal Function: The pharmacokinetics of tenofovir are altered in patients with renal impairment [See Warnings and Precautions (5.3)]. In patients with creatinine clearance <50 mL/min or with end-stage renal disease (ESRD) requiring dialysis, Cmax, and AUC0–∞ of tenofovir were increased (Table 9). It is recommended that the dosing interval for VIREAD be modified in patients with creatinine clearance <50 mL/min or in patients with ESRD who require dialysis [See Dosage and Administration (2.2)].

Table 9 Pharmacokinetic Parameters (Mean ± SD) of Tenofovir [300 mg, single dose of VIREAD] in Patients with Varying Degrees of Renal Function
Baseline Creatinine Clearance (mL/min) | >80 (N=3) | 50–80 (N=10) | 30–49 (N=8) | 12–29 (N=11)
Cmax (µg/mL) | 0.34 ± 0.03 | 0.33 ± 0.06 | 0.37 ± 0.16 | 0.60 ± 0.19
AUC0–∞ (µg∙hr/mL) | 2.18 ± 0.26 | 3.06 ± 0.93 | 6.01 ± 2.50 | 15.98 ± 7.22
CL/F (mL/min) | 1043.7 ± 115.4 | 807.7 ± 279.2 | 444.4 ± 209.8 | 177.0 ± 97.1
CLrenal (mL/min) | 243.5 ± 33.3 | 168.6 ± 27.5 | 100.6 ± 27.5 | 43.0 ± 31.2

Tenofovir is efficiently removed by hemodialysis with an extraction coefficient of approximately 54%. Following a single 300 mg dose of VIREAD, a four-hour hemodialysis session removed approximately 10% of the administered tenofovir dose.

Patients with Hepatic Impairment: The pharmacokinetics of tenofovir following a 300 mg single dose of VIREAD have been studied in non-HIV infected patients with moderate to severe hepatic impairment. There were no substantial alterations in tenofovir pharmacokinetics in patients with hepatic impairment compared with unimpaired patients. No change in VIREAD dosing is required in patients with hepatic impairment.

Assessment of Drug Interactions

At concentrations substantially higher (~300-fold) than those observed in vivo, tenofovir did not inhibit in vitro drug metabolism mediated by any of the following human CYP isoforms: CYP3A4, CYP2D6, CYP2C9, or CYP2E1. However, a small (6%) but statistically significant reduction in metabolism of CYP1A substrate was observed. Based on the results of in vitro experiments and the known elimination pathway of tenofovir, the potential for CYP mediated interactions involving tenofovir with other medicinal products is low [See Clinical Pharmacology (12.3)].

VIREAD has been evaluated in healthy volunteers in combination with abacavir, atazanavir, didanosine, efavirenz, emtricitabine, entecavir, indinavir, lamivudine, lopinavir/ritonavir, methadone, nelfinavir, oral contraceptives, ribavirin, saquinavir/ritonavir, and tacrolimus. Tables 10 and 11 summarize pharmacokinetic effects of coadministered drug on tenofovir pharmacokinetics and effects of VIREAD on the pharmacokinetics of coadministered drug.

Table 10 Drug Interactions: Changes in Pharmacokinetic Parameters for Tenofovir [Patients received VIREAD 300 mg once daily.] in the Presence of the Coadministered Drug
Coadministered Drug | Dose of Coadministered Drug (mg) | N | % Change of Tenofovir Pharmacokinetic Parameters [Increase = ↑; Decrease = ↓; No Effect = ; NC = Not Calculated] (90% CI)
Coadministered Drug | Dose of Coadministered Drug (mg) | N | Cmax | AUC | Cmin
Abacavir | 300 once | 8 |  |  | NC
Atazanavir [Reyataz Prescribing Information] | 400 once daily × 14 days | 33 | ↑ 14 (↑ 8 to ↑ 20) | ↑ 24 (↑ 21 to ↑ 28) | ↑ 22 (↑ 15 to ↑ 30)
Didanosine (enteric-coated) | 400 once | 25
Didanosine (buffered) | 250 or 400 once daily × 7 days | 14
Efavirenz | 600 once daily × 14 days | 29
Emtricitabine | 200 once daily × 7 days | 17
Entecavir | 1 mg once daily × 10 days | 28
Indinavir | 800 three times daily × 7 days | 13 | ↑ 14 (↓ 3 to ↑ 33)
Lamivudine | 150 twice daily × 7 days | 15
Lopinavir/Ritonavir | 400/100 twice daily × 14 days | 24 |  | ↑ 32 (↑ 25 to ↑ 38) | ↑ 51 (↑ 37 to ↑ 66)
Nelfinavir | 1250 twice daily × 14 days | 29
Saquinavir/Ritonavir | 1000/100 twice daily × 14 days | 35 |  |  | ↑ 23 (↑ 16 to ↑ 30)
Tacrolimus | 0.05 mg/kg twice daily × 7 days | 21 | ↑ 13 (↑ 1 to ↑ 27)

Following multiple dosing to HIV- and HBV-negative subjects receiving either chronic methadone maintenance therapy or oral contraceptives, or single doses of ribavirin, steady state tenofovir pharmacokinetics were similar to those observed in previous studies, indicating lack of clinically significant drug interactions between these agents and VIREAD.

Table 11 Drug Interactions: Changes in Pharmacokinetic Parameters for Coadministered Drug in the Presence of VIREAD
Coadministered Drug | Dose of Coadministered Drug (mg) | N | % Change of Coadministered Drug Pharmacokinetic Parameters [Increase = ↑; Decrease = ↓; No Effect = ; NA = Not Applicable] (90% CI)
Coadministered Drug | Dose of Coadministered Drug (mg) | N | Cmax | AUC | Cmin
Abacavir | 300 once | 8 | ↑ 12 (↓ 1 to ↑ 26) |  | NA
Atazanavir [Reyataz Prescribing Information] | 400 once daily × 14 days | 34 | ↓ 21 (↓ 27 to ↓ 14) | ↓ 25 (↓ 30 to ↓ 19) | ↓ 40 (↓ 48 to ↓ 32)
Atazanavir | Atazanavir/ Ritonavir 300/100 once daily × 42 days | 10 | ↓ 28 (↓ 50 to ↑ 5) | ↓ 25 [In HIV-infected patients, addition of tenofovir DF to atazanavir 300 mg plus ritonavir 100 mg, resulted in AUC and Cmin values of atazanavir that were 2.3- and 4-fold higher than the respective values observed for atazanavir 400 mg when given alone.] (↓ 42 to ↓ 3) | ↓ 23 (↓ 46 to ↑ 10)
Efavirenz | 600 once daily × 14 days | 30
Emtricitabine | 200 once daily × 7 days | 17 |  |  | ↑ 20 (↑ 12 to ↑ 29)
Entecavir | 1 mg once daily × 10 days | 28 |  | ↑ 13 (↑ 11 to ↑ 15)
Indinavir | 800 three times daily × 7 days | 12 | ↓ 11 (↓ 30 to ↑ 12)
Lamivudine | 150 twice daily × 7 days | 15 | ↓ 24 (↓ 34 to ↓ 12)
Lopinavir | Lopinavir/Ritonavir 400/100 twice daily × 14 days | 24
Ritonavir | Lopinavir/Ritonavir 400/100 twice daily × 14 days | 24
Methadone [R-(active), S- and total methadone exposures were equivalent when dosed alone or with VIREAD.] | 40–110 once daily × 14 days [Individual subjects were maintained on their stable methadone dose. No pharmacodynamic alterations (opiate toxicity or withdrawal signs or symptoms) were reported.] | 13
Nelfinavir | 1250 twice daily × 14 days | 29
M8 metabolite | 1250 twice daily × 14 days | 29
Oral Contraceptives [Ethinyl estradiol and 17-deacetyl norgestimate (pharmacologically active metabolite) exposures were equivalent when dosed alone or with VIREAD.] | Ethinyl Estradiol/ Norgestimate (Ortho-Tricyclen) once daily × 7 days | 20
Ribavirin | 600 once | 22 |  |  | NA
Saquinavir | Saquinavir/Ritonavir 1000/100 twice daily × 14 days | 32 | ↑ 22 (↑ 6 to ↑ 41) | ↑ 29 [Increases in AUC and Cmin are not expected to be clinically relevant; hence no dose adjustments are required when tenofovir DF and ritonavir-boosted saquinavir are coadministered.] (↑ 12 to ↑ 48) | ↑ 47 (↑ 23 to ↑ 76)
Ritonavir | Saquinavir/Ritonavir 1000/100 twice daily × 14 days | 32 |  |  | ↑ 23 (↑ 3 to ↑ 46)
Tacrolimus | 0.05 mg/kg twice daily × 7 days | 21

Table 12 summarizes the drug interaction between VIREAD and didanosine. Coadministration of VIREAD and didanosine should be undertaken with caution [See Drug Interactions (7.1)]. When administered with multiple doses of VIREAD, the Cmax and AUC of didanosine 400 mg increased significantly. The mechanism of this interaction is unknown. When didanosine 250 mg enteric-coated capsules were administered with VIREAD, systemic exposures to didanosine were similar to those seen with the 400 mg enteric-coated capsules alone under fasted conditions.

Table 12 Drug Interactions: Pharmacokinetic Parameters for Didanosine in the Presence of VIREAD
Didanosine Dose (mg)/ Method of Administration | VIREAD Method of Administration [Administration with food was with a light meal (~373 kcal, 20% fat).] | N | % Difference (90% CI) vs. Didanosine 400 mg Alone, Fasted [Increase = ↑; Decrease = ↓; No Effect =]
Didanosine Dose (mg)/ Method of Administration | VIREAD Method of Administration [Administration with food was with a light meal (~373 kcal, 20% fat).] | N | Cmax | AUC
Buffered tablets
400 once daily [Includes 4 subjects weighing <60 kg receiving ddI 250 mg.] × 7 days | Fasted 1 hour after didanosine | 14 | ↑ 28 (↑ 11 to ↑ 48) | ↑ 44 (↑ 31 to ↑ 59)
Enteric coated capsules
400 once, fasted | With food, 2 hours after didanosine | 26 | ↑ 48 (↑ 25 to ↑ 76) | ↑ 48 (↑ 31 to ↑ 67)
400 once, with food | Simultaneously with didanosine | 26 | ↑ 64 (↑ 41 to ↑ 89) | ↑ 60 (↑ 44 to ↑ 79)
250 once, fasted | With food, 2 hours after didanosine | 28 | ↓ 10 (↓ 22 to ↑ 3)
250 once, fasted | Simultaneously with didanosine | 28 |  | ↑ 14 (0 to ↑ 31)
250 once, with food | Simultaneously with didanosine | 28 | ↓ 29 (↓ 39 to ↓ 18) | ↓ 11 (↓ 23 to ↑ 2)

Mechanism of Action

Tenofovir disoproxil fumarate is an acyclic nucleoside phosphonate diester analog of adenosine monophosphate. Tenofovir disoproxil fumarate requires initial diester hydrolysis for conversion to tenofovir and subsequent phosphorylations by cellular enzymes to form tenofovir diphosphate, an obligate chain terminator. Tenofovir diphosphate inhibits the activity of HIV-1 reverse transcriptase and HBV polymerase by competing with the natural substrate deoxyadenosine 5'-triphosphate and, after incorporation into DNA, by DNA chain termination. Tenofovir diphosphate is a weak inhibitor of mammalian DNA polymerases α, β, and mitochondrial DNA polymerase γ.

Activity against HIV

Antiviral Activity

The antiviral activity of tenofovir against laboratory and clinical isolates of HIV-1 was assessed in lymphoblastoid cell lines, primary monocyte/macrophage cells and peripheral blood lymphocytes. The EC50 (50% effective concentration) values for tenofovir were in the range of 0.04 µM to 8.5 µM. In drug combination studies of tenofovir with nucleoside reverse transcriptase inhibitors (abacavir, didanosine, lamivudine, stavudine, zalcitabine, zidovudine), non-nucleoside reverse transcriptase inhibitors (delavirdine, efavirenz, nevirapine), and protease inhibitors (amprenavir, indinavir, nelfinavir, ritonavir, saquinavir), additive to synergistic effects were observed. Tenofovir displayed antiviral activity in cell culture against HIV-1 clades A, B, C, D, E, F, G, and O (EC50 values ranged from 0.5 µM to 2.2 µM) and strain specific activity against HIV-2 (EC50 values ranged from 1.6 µM to 5.5 µM).

Resistance

HIV-1 isolates with reduced susceptibility to tenofovir have been selected in cell culture. These viruses expressed a K65R substitution in reverse transcriptase and showed a 2–4 fold reduction in susceptibility to tenofovir.

In Study 903 of treatment-naïve patients (VIREAD + lamivudine + efavirenz versus stavudine + lamivudine + efavirenz) [See Clinical Studies (14.1)], genotypic analyses of isolates from patients with virologic failure through Week 144 showed development of efavirenz and lamivudine resistance-associated substitutions to occur most frequently and with no difference between the treatment arms. The K65R substitution occurred in 8/47 (17%) analyzed patient isolates on the VIREAD arm and in 2/49 (4%) analyzed patient isolates on the stavudine arm. Of the 8 patients whose virus developed K65R in the VIREAD arm through 144 weeks, 7 of these occurred in the first 48 weeks of treatment and one at Week 96. Other substitutions resulting in resistance to VIREAD were not identified in this study.

In Study 934 of treatment-naïve patients (VIREAD + EMTRIVA + efavirenz versus zidovudine (AZT)/lamivudine (3TC) + efavirenz) [See Clinical Studies (14.1)], genotypic analysis performed on HIV-1 isolates from all confirmed virologic failure patients with >400 copies/mL of HIV-1 RNA at Week 144 or early discontinuation showed development of efavirenz resistance-associated substitutions occurred most frequently and was similar between the two treatment arms. The M184V substitution, associated with resistance to EMTRIVA and lamivudine, was observed in 2/19 analyzed patient isolates in the VIREAD + EMTRIVA group and in 10/29 analyzed patient isolates in the zidovudine/lamivudine group. Through 144 weeks of Study 934, no patients have developed a detectable K65R substitution in their HIV-1 as analyzed through standard genotypic analysis.

Cross Resistance

Cross-resistance among certain reverse transcriptase inhibitors has been recognized. The K65R substitution selected by tenofovir is also selected in some HIV-1 infected subjects treated with abacavir, didanosine, or zalcitabine. HIV-1 isolates with this mutation also show reduced susceptibility to emtricitabine and lamivudine. Therefore, cross-resistance among these drugs may occur in patients whose virus harbors the K65R substitution. HIV-1 isolates from patients (N=20) whose HIV-1 expressed a mean of 3 zidovudine-associated reverse transcriptase substitutions (M41L, D67N, K70R, L210W, T215Y/F, or K219Q/E/N), showed a 3.1-fold decrease in the susceptibility to tenofovir. Multinucleoside resistant HIV-1 with a T69S double insertion substitution in the reverse transcriptase showed reduced susceptibility to tenofovir.

In Studies 902 and 907 conducted in treatment-experienced patients (VIREAD + Standard Background Therapy (SBT) compared to Placebo + SBT) [See Clinical Studies (14.1)], 14/304 (5%) of the VIREAD-treated patients with virologic failure through Week 96 had >1.4-fold (median 2.7-fold) reduced susceptibility to tenofovir. Genotypic analysis of the baseline and failure isolates showed the development of the K65R substitution in the HIV-1 reverse transcriptase gene.

The virologic response to VIREAD therapy has been evaluated with respect to baseline viral genotype (N=222) in treatment-experienced patients participating in Studies 902 and 907.

In these clinical studies, 94% of the participants evaluated had baseline HIV-1 isolates expressing at least one NRTI mutation. These included resistance substitutions associated with zidovudine (M41L, D67N, K70R, L210W, T215Y/F, or K219Q/E/N), the abacavir/emtricitabine/lamivudine resistance-associated substitution (M184V), and others. In addition the majority of participants evaluated had substitutions associated with either PI or NNRTI use. Virologic responses for patients in the genotype substudy were similar to the overall study results.

Several exploratory analyses were conducted to evaluate the effect of specific substitutions and substitutional patterns on virologic outcome. Because of the large number of potential comparisons, statistical testing was not conducted. Varying degrees of cross-resistance of VIREAD to pre-existing zidovudine resistance-associated substitutions were observed and appeared to depend on the number of specific substitutions. VIREAD-treated patients whose HIV-1 expressed 3 or more zidovudine resistance-associated substitutions that included either the M41L or L210W reverse transcriptase substitution showed reduced responses to VIREAD therapy; however, these responses were still improved compared with placebo. The presence of the D67N, K70R, T215Y/F, or K219Q/E/N substitution did not appear to affect responses to VIREAD therapy.

In the protocol defined analyses, virologic response to VIREAD was not reduced in patients with HIV-1 that expressed the abacavir/emtricitabine/lamivudine resistance-associated M184V substitution. In the presence of zidovudine resistance-associated substitutions, the M184V substitution did not affect the mean HIV-1 RNA responses to VIREAD treatment. HIV-1 RNA responses among these patients were durable through Week 48.

Studies 902 and 907 Phenotypic Analyses

The virologic response to VIREAD therapy has been evaluated with respect to baseline phenotype (N=100) in treatment-experienced patients participating in two controlled trials. Phenotypic analysis of baseline HIV-1 from patients in these studies demonstrated a correlation between baseline susceptibility to VIREAD and response to VIREAD therapy. Table 13 summarizes the HIV-1 RNA response by baseline VIREAD susceptibility.

Table 13 HIV-1 RNA Response at Week 24 by Baseline VIREAD Susceptibility (Intent-To-Treat) [Tenofovir susceptibility was determined by recombinant phenotypic Antivirogram assay (Virco).]
Baseline VIREAD Susceptibility [Fold change in susceptibility from wild-type.] | Change in HIV-1 RNA [Average HIV-1 RNA change from baseline through Week 24 (DAVG24) in log10 copies/mL.] (N)
<1 | -0.74 (35)
>1 and ≤3 | -0.56 (49)
>3 and ≤4 | -0.3 (7)
>4 | -0.12 (9)

Activity against HBV

Antiviral Activity

The antiviral activity of tenofovir against HBV was assessed in the HepG2 2.2.15 cell line. The EC50 values for tenofovir ranged from 0.14 to 1.5 µM, with CC50 (50% cytotoxicity concentration) values >100 µM. In cell culture combination antiviral activity studies of tenofovir with the nucleoside anti-HBV reverse transcriptase inhibitors emtricitabine, entecavir, lamivudine and telbivudine, no antagonistic activity was observed.

Resistance

Out of 426 HBeAg negative and HBeAg positive patients, 39 patients had serum HBV DNA >400 copies/mL at Week 48. Genotypic data from paired baseline and on treatment isolates were available for 28 of the 39 patients. No specific amino acid substitutions occurred in these subjects' isolates at sufficient frequency to establish an association with tenofovir resistance.

Cross Resistance

Cross-resistance has been observed among HBV reverse transcriptase inhibitors.

In cell based assays, HBV strains expressing the rtV173L, rtL180M, and rtM204I/V substitutions associated with resistance to lamivudine and telbivudine showed a susceptibility to tenofovir ranging from 0.7 to 3.4-fold that of wild type virus. The rtL180M and rtM204I/V double substitutions conferred 3.4-fold reduced susceptibility to tenofovir.

HBV strains expressing the rtL180M, rtT184G, rtS202G/I, rtM204V, and rtM250V substitutions associated with resistance to entecavir showed a susceptibility to tenofovir ranging from 0.6 to 6.9-fold that of wild type virus. An HBV strain expressing rtL180M, rtT184G, rtS202I and rtM204V together had a 6.9-fold reduction in susceptibility to tenofovir.

HBV strains expressing the adefovir-associated resistance substitutions rtA181V and/or rtN236T showed reductions in susceptibility to tenofovir ranging from 2.9 to 10-fold that of wild type virus.

Strains containing the rtA181T substitution showed changes in susceptibility to tenofovir ranging from 0.9 to 1.5-fold that of wild type virus.

13 NONCLINICAL TOXICOLOGY

13.1 Carcinogenesis, Mutagenesis, Impairment of Fertility

Long-term oral carcinogenicity studies of tenofovir disoproxil fumarate in mice and rats were carried out at exposures up to approximately 16 times (mice) and 5 times (rats) those observed in humans at the therapeutic dose for HIV-1 infection. At the high dose in female mice, liver adenomas were increased at exposures 16 times that in humans. In rats, the study was negative for carcinogenic findings at exposures up to 5 times that observed in humans at the therapeutic dose.

Tenofovir disoproxil fumarate was mutagenic in the in vitro mouse lymphoma assay and negative in an in vitro bacterial mutagenicity test (Ames test). In an in vivo mouse micronucleus assay, tenofovir disoproxil fumarate was negative when administered to male mice.

There were no effects on fertility, mating performance or early embryonic development when tenofovir disoproxil fumarate was administered to male rats at a dose equivalent to 10 times the human dose based on body surface area comparisons for 28 days prior to mating and to female rats for 15 days prior to mating through day seven of gestation. There was, however, an alteration of the estrous cycle in female rats.

13.2 Animal Toxicology and/or Pharmacology

Tenofovir and tenofovir disoproxil fumarate administered in toxicology studies to rats, dogs, and monkeys at exposures (based on AUCs) greater than or equal to 6 fold those observed in humans caused bone toxicity. In monkeys the bone toxicity was diagnosed as osteomalacia. Osteomalacia observed in monkeys appeared to be reversible upon dose reduction or discontinuation of tenofovir. In rats and dogs, the bone toxicity manifested as reduced bone mineral density. The mechanism(s) underlying bone toxicity is unknown.

Evidence of renal toxicity was noted in 4 animal species. Increases in serum creatinine, BUN, glycosuria, proteinuria, phosphaturia, and/or calciuria and decreases in serum phosphate were observed to varying degrees in these animals. These toxicities were noted at exposures (based on AUCs) 2–20 times higher than those observed in humans. The relationship of the renal abnormalities, particularly the phosphaturia, to the bone toxicity is not known.

14 CLINICAL STUDIES

Treatment-Naïve Patients

Study 903

Data through 144 weeks are reported for Study 903, a double-blind, active-controlled multicenter study comparing VIREAD (300 mg once daily) administered in combination with lamivudine and efavirenz versus stavudine (d4T), lamivudine, and efavirenz in 600 antiretroviral-naïve patients. Patients had a mean age of 36 years (range 18–64), 74% were male, 64% were Caucasian and 20% were Black. The mean baseline CD4^+ cell count was 279 cells/mm^3 (range 3–956) and median baseline plasma HIV-1 RNA was 77,600 copies/mL (range 417–5,130,000). Patients were stratified by baseline HIV-1 RNA and CD4^+ cell count. Forty-three percent of patients had baseline viral loads >100,000 copies/mL and 39% had CD4^+ cell counts <200 cells/mm^3. Treatment outcomes through 48 and 144 weeks are presented in Table 14.

Table 14 Outcomes of Randomized Treatment at Week 48 and 144 (Study 903)
 | At Week 48 |  | At Week 144
Outcomes | VIREAD+3TC +EFV (N=299) | d4T+3TC +EFV (N=301) | VIREAD+3TC +EFV (N=299) | d4T+3TC +EFV (N=301)
Responder [Patients achieved and maintained confirmed HIV-1 RNA <400 copies/mL through Week 48 and 144.] | 79% | 82% | 68% | 62%
Virologic failure [Includes confirmed viral rebound and failure to achieve confirmed <400 copies/mL through Week 48 and 144.] | 6% | 4% | 10% | 8%
Rebound | 5% | 3% | 8% | 7%
Never suppressed | 0% | 1% | 0% | 0%
Added an antiretroviral agent | 1% | 1% | 2% | 1%
Death | <1% | 1% | <1% | 2%
Discontinued due to adverse event | 6% | 6% | 8% | 13%
Discontinued for other reasons [Includes lost to follow-up, patient's withdrawal, noncompliance, protocol violation and other reasons.] | 8% | 7% | 14% | 15%

Achievement of plasma HIV-1 RNA concentrations of less than 400 copies/mL at Week 144 was similar between the two treatment groups for the population stratified at baseline on the basis of HIV-1 RNA concentration (> or ≤100,000 copies/mL) and CD4^+ cell count (< or ≥200 cells/mm^3). Through 144 weeks of therapy, 62% and 58% of patients in the VIREAD and stavudine arms, respectively achieved and maintained confirmed HIV-1 RNA <50 copies/mL. The mean increase from baseline in CD4^+ cell count was 263 cells/mm^3 for the VIREAD arm and 283 cells/mm^3 for the stavudine arm.

Through 144 weeks, 11 patients in the VIREAD group and 9 patients in the stavudine group experienced a new CDC Class C event.

Study 934

Data through 144 weeks are reported for Study 934, a randomized, open-label, active-controlled multicenter study comparing emtricitabine + VIREAD administered in combination with efavirenz versus zidovudine/lamivudine fixed-dose combination administered in combination with efavirenz in 511 antiretroviral-naïve patients. From Weeks 96 to 144 of the study, patients received a fixed-dose combination of emtricitabine and tenofovir DF with efavirenz in place of emtricitabine + VIREAD with efavirenz. Patients had a mean age of 38 years (range 18–80), 86% were male, 59% were Caucasian and 23% were Black. The mean baseline CD4^+ cell count was 245 cells/mm^3 (range 2–1191) and median baseline plasma HIV-1 RNA was 5.01 log10 copies/mL (range 3.56–6.54). Patients were stratified by baseline CD4^+ cell count (< or ≥200 cells/mm^3); 41% had CD4^+ cell counts <200 cells/mm^3 and 51% of patients had baseline viral loads >100,000 copies/mL. Treatment outcomes through 48 and 144 weeks for those patients who did not have efavirenz resistance at baseline are presented in Table 15.

Table 15 Outcomes of Randomized Treatment at Week 48 and 144 (Study 934)
Outcomes | At Week 48 |  | At Week 144
Outcomes | FTC +VIREAD +EFV (N=244) | AZT/3TC +EFV (N=243) | FTC +VIREAD +EFV (N=227) [Patients who were responders at Week 48 or Week 96 (HIV-1 RNA <400 copies/mL) but did not consent to continue study after Week 48 or Week 96 were excluded from analysis.] | AZT/3TC +EFV (N=229)
Responder [Patients achieved and maintained confirmed HIV-1 RNA <400 copies/mL through Weeks 48 and 144.] | 84% | 73% | 71% | 58%
Virologic failure [Includes confirmed viral rebound and failure to achieve confirmed <400 copies/mL through Weeks 48 and 144.] | 2% | 4% | 3% | 6%
Rebound | 1% | 3% | 2% | 5%
Never suppressed | 0% | 0% | 0% | 0%
Change in antiretroviral regimen | 1% | 1% | 1% | 1%
Death | <1% | 1% | 1% | 1%
Discontinued due to adverse event | 4% | 9% | 5% | 12%
Discontinued for other reasons [Includes lost to follow-up, patient withdrawal, noncompliance, protocol violation and other reasons.] | 10% | 14% | 20% | 22%

Through Week 48, 84% and 73% of patients in the emtricitabine + VIREAD group and the zidovudine/lamivudine group, respectively, achieved and maintained HIV-1 RNA <400 copies/mL (71% and 58% through Week 144). The difference in the proportion of patients who achieved and maintained HIV-1 RNA <400 copies/mL through 48 weeks largely results from the higher number of discontinuations due to adverse events and other reasons in the zidovudine/lamivudine group in this open-label study. In addition, 80% and 70% of patients in the emtricitabine + VIREAD group and the zidovudine/lamivudine group, respectively, achieved and maintained HIV-1 RNA <50 copies/mL through Week 48 (64% and 56% through Week 144). The mean increase from baseline in CD4^+ cell count was 190 cells/mm^3 in the EMTRIVA + VIREAD group and 158 cells/mm^3 in the zidovudine/lamivudine group at Week 48 (312 and 271 cells/mm^3 at Week 144).

Through 48 weeks, 7 patients in the emtricitabine + VIREAD group and 5 patients in the zidovudine/lamivudine group experienced a new CDC Class C event (10 and 6 patients through 144 weeks).

Treatment-Experienced Patients

Study 907

Study 907 was a 24-week, double-blind placebo-controlled multicenter study of VIREAD added to a stable background regimen of antiretroviral agents in 550 treatment-experienced patients. After 24 weeks of blinded study treatment, all patients continuing on study were offered open-label VIREAD for an additional 24 weeks. Patients had a mean baseline CD4^+ cell count of 427 cells/mm^3 (range 23–1385), median baseline plasma HIV-1 RNA of 2340 (range 50–75,000) copies/mL, and mean duration of prior HIV-1 treatment was 5.4 years. Mean age of the patients was 42 years, 85% were male and 69% were Caucasian, 17% Black and 12% Hispanic.

Changes from baseline in log10 copies/mL plasma HIV-1 RNA levels over time up to Week 48 are presented below in Figure 1.

The percent of patients with HIV-1 RNA <400 copies/mL and outcomes of patients through 48 weeks are summarized in Table 16.

Table 16 Outcomes of Randomized Treatment (Study 907)
Outcomes | 0–24 weeks |  | 0–48 weeks | 24–48 weeks
Outcomes | VIREAD (N=368) | Placebo (N=182) | VIREAD (N=368) | Placebo Crossover to VIREAD (N=170)
HIV-1 RNA <400 copies/mL [Patients with HIV-1 RNA <400 copies/mL and no prior study drug discontinuation at Week 24 and 48 respectively.] | 40% | 11% | 28% | 30%
Virologic failure [Patients with HIV-1 RNA ≥400 copies/mL efficacy failure or missing HIV-1 RNA at Week 24 and 48 respectively.] | 53% | 84% | 61% | 64%
Discontinued due to adverse event | 3% | 3% | 5% | 5%
Discontinued for other reasons [Includes lost to follow-up, patient withdrawal, noncompliance, protocol violation and other reasons.] | 3% | 3% | 5% | 1%

At 24 weeks of therapy, there was a higher proportion of patients in the VIREAD arm compared to the placebo arm with HIV-1 RNA <50 copies/mL (19% and 1%, respectively). Mean change in absolute CD4^+ cell counts by Week 24 was +11 cells/mm^3 for the VIREAD group and -5 cells/mm^3 for the placebo group. Mean change in absolute CD4^+ cell counts by Week 48 was +4 cells/mm^3 for the VIREAD group.

Through Week 24, one patient in the VIREAD group and no patients in the placebo arm experienced a new CDC Class C event.

HBeAg-Negative Chronic Hepatitis B

Study 0102 was a Phase 3, randomized, double-blind, active-controlled study of VIREAD 300 mg compared to HEPSERA 10 mg in 375 HBeAg- (anti-HBe+) patients with compensated liver function, the majority of whom were nucleoside-naïve. The mean age of patients was 44 years, 77% were male, 25% were Asian, 65% were Caucasian, 17% had previously received alpha-interferon therapy and 18% were nucleoside-experienced (16% had prior lamivudine experience). At baseline, patients had a mean Knodell necroinflammatory score of 7.8; mean plasma HBV DNA was 6.9 log10 copies/mL; and mean serum ALT was 140 U/L.

HBeAg-Positive Chronic Hepatitis B

Study 0103 was a Phase 3, randomized, double-blind, active-controlled study of VIREAD 300 mg compared to HEPSERA 10 mg in 266 HBeAg+ nucleoside-naïve patients with compensated liver function. The mean age of patients was 34 years, 69% were male, 36% were Asian, 52% were Caucasian, 16% had previously received alpha-interferon therapy, and <5% were nucleoside experienced. At baseline, patients had a mean Knodell necroinflammatory score of 8.4; mean plasma HBV DNA was 8.7 log10 copies /mL; and mean serum ALT was 147 U/L.

The primary data analysis was conducted after all patients reached 48 weeks of treatment and results are summarized below.

The primary efficacy endpoint in both studies was complete response to treatment defined as HBV DNA <400 copies/mL and Knodell necroinflammatory score improvement of at least 2 points, without worsening in Knodell fibrosis at Week 48 (Table 17).

Table 17 Histological, Virological, Biochemical, and Serological Response at Week 48
 | 0102 (HBeAg-) |  | 0103 (HBeAg+)
 | VIREAD (N=250) | HEPSERA (N=125) | VIREAD (N=176) | HEPSERA (N=90)
Complete Response | 71% | 49% | 67% | 12%
Histology
Histological Response [Knodell necroinflammatory score improvement of at least 2 points without worsening in Knodell fibrosis.] | 72% | 69% | 74% | 68%
HBV DNA <400 copies/mL (<69 IU/mL) | 93% | 63% | 76% | 13%
ALT Normalized ALT [The population used for analysis of ALT normalization included only patients with ALT above ULN at baseline.] | 76% | 77% | 68% | 54%
Serology HBeAg Loss/Seroconversion | NA [NA = Not Applicable] | NA | 20%/19% | 16%/16%
HBsAg Loss/Seroconversion | 0/0 | 0/0 | 3%/1% | 0/0

A small proportion of nucleoside-experienced patients received VIREAD in the clinical trials: 43 patients in Study 0102 and 8 patients in Study 0103. Across both studies, 5 patients had HBV containing lamivudine-resistance associated substitutions at baseline. The numbers of patients in these subgroups were too small to establish efficacy.

16 HOW SUPPLIED/STORAGE AND HANDLING

The almond-shaped, light blue, film-coated tablets contain 300 mg of tenofovir disoproxil fumarate, which is equivalent to 245 mg of tenofovir disoproxil, are debossed with "GILEAD" and "4331" on one side and with "300" on the other side, and are available in unit of use bottles (containing a desiccant [silica gel canister or sachet] and closed with a child-resistant closure) of:

They are supplied by State of Florida DOH Central Pharmacy as follows:

NDC | Strength | Quantity/Form | Color | Source Prod. Code
53808-0810-1 | 300 mg | 30 Tablets in a Blister Pack | Light Blue | 61958-0401

STORAGE AND HANDLING

Store at 25 °C (77 °F), excursions permitted to 15–30 °C (59–86 °F) (see USP Controlled Room Temperature).

Do not use if seal over bottle opening is broken or missing.

17 PATIENT COUNSELING INFORMATION

See FDA-approved patient labeling (17.2)

17.1 Information for Patients

Patients should be advised that:

- VIREAD is not a cure for HIV-1 infection and patients may continue to experience illnesses associated with HIV-1 infection, including opportunistic infections. Patients should remain under the care of a physician when using VIREAD.
- The use of VIREAD has not been shown to reduce the risk of transmission of HIV-1 or HBV to others through sexual contact or blood contamination.
- The long term effects of VIREAD are unknown.
- VIREAD Tablets are for oral ingestion only.
- VIREAD should not be discontinued without first informing their physician.
- If you have HIV-1 infection, with or without HBV coinfection, it is important to take VIREAD with combination therapy.
- It is important to take VIREAD on a regular dosing schedule and to avoid missing doses.
- Lactic acidosis and severe hepatomegaly with steatosis, including fatal cases, have been reported. Treatment with VIREAD should be suspended in any patient who develops clinical symptoms suggestive of lactic acidosis or pronounced hepatotoxicity (including nausea, vomiting, unusual or unexpected stomach discomfort, and weakness) [See Warnings and Precautions (5.1)].
- Patients with HIV-1 should be tested for Hepatitis B virus (HBV) before initiating antiretroviral therapy [See Warnings and Precautions (5.5)].
- Severe acute exacerbations of hepatitis have been reported in patients who are infected with HBV or coinfected with HBV and HIV-1 and have discontinued VIREAD [See Warnings and Precautions (5.2)].
- In patients with chronic hepatitis B, it is important to obtain HIV antibody testing prior to initiating VIREAD [See Warnings and Precautions (5.5)].
- Renal impairment, including cases of acute renal failure and Fanconi syndrome, has been reported. VIREAD should be avoided with concurrent or recent use of a nephrotoxic agent [See Warnings and Precautions (5.3)]. Dosing interval of VIREAD may need adjustment in patients with renal impairment [See Dosage and Administration (2.2)].
- VIREAD should not be coadministered with the fixed-dose combination products TRUVADA and ATRIPLA since it is a component of these products [See Warnings and Precautions (5.4)].
- VIREAD should not be administered in combination with HEPSERA [See Warnings and Precautions (5.4)].
- Decreases in bone mineral density have been observed with the use of VIREAD in patients with HIV. Bone mineral density monitoring should be considered in patients who have a history of pathologic bone fracture or at risk for osteopenia [See Warnings and Precautions (5.6)].
- In the treatment of chronic hepatitis B, the optimal duration of treatment is unknown. The relationship between response and long-term prevention of outcomes such as hepatocellular carcinoma is not known.

PATIENT INFORMATION

VIREAD® (VEER ee ad) Tablets

Generic Name: tenofovir disoproxil fumarate (te NOE' fo veer dye soe PROX il FYOU-mar-ate)

Read this leaflet carefully before you start taking VIREAD. Also, read it each time you get your VIREAD prescription refilled, in case something has changed. This information does not take the place of talking with your healthcare provider when you start this medicine and at check ups. You should stay under a healthcare provider's care when taking VIREAD. Do not change or stop your medicine without first talking with your healthcare provider. Talk to your healthcare provider if you have any questions about VIREAD.

What is VIREAD and how does it work?

VIREAD is a type of medicine called a nucleotide analog reverse transcriptase and HBV polymerase inhibitor (NRTI).

Use in the Treatment of HIV-1 Infection:

VIREAD is a treatment for Human Immunodeficiency Virus (HIV) infection in adults age 18 years and older. VIREAD is always used in combination with other anti-HIV-1 medicines to treat people with HIV-1 infection.

HIV infection destroys CD4^+ T cells, which are important to the immune system. After a large number of T cells are destroyed, acquired immune deficiency syndrome (AIDS) develops.

VIREAD helps to block HIV-1 reverse transcriptase, a chemical in your body (enzyme) that is needed for HIV-1 to multiply. VIREAD lowers the amount of HIV-1 in the blood (called viral load) and may help to increase the number of T cells (called CD4^+ cells). Lowering the amount of HIV-1 in the blood lowers the chance of death or infections that happen when your immune system is weak (opportunistic infections).

Use in the Treatment of Chronic Hepatitis B:

VIREAD is also used to treat chronic hepatitis B (an infection with hepatitis B virus [HBV]) in adults age 18 years and older. VIREAD works by interfering with the normal working of an enzyme (HBV DNA polymerase) that is essential for the HBV virus to reproduce itself. VIREAD may help lower the amount of hepatitis B virus in your body by lowering the ability of the virus to multiply and infect new liver cells.

Does VIREAD cure HIV-1 or AIDS?

VIREAD does not cure HIV-1 infection or AIDS. The long-term effects of VIREAD are not known at this time. People taking VIREAD may still get opportunistic infections or other conditions that happen with HIV-1 infection. Opportunistic infections are infections that develop because the immune system is weak. Some of these conditions are pneumonia, herpes virus infections, and Mycobacterium avium complex (MAC) infections.

We do not know how long VIREAD may help your hepatitis. Sometimes viruses change in your body and medicines no longer work. This is called drug resistance.

We do not know if VIREAD will reduce your chances of getting liver cancer from chronic hepatitis B.

Does VIREAD reduce the risk of passing HIV-1 or HBV to others?

VIREAD does not reduce the risk of passing HIV-1 or HBV to others through sexual contact or blood contamination. Continue to practice safe sex and do not use or share dirty needles.

Who should not take VIREAD?

Together with your healthcare provider, you need to decide whether VIREAD is right for you.

Do not take VIREAD if

- you are allergic to VIREAD or any of its ingredients
- you are already taking TRUVADA® or ATRIPLA® because VIREAD is one of the active ingredients in TRUVADA and ATRIPLA
- you have not already discontinued treatment with HEPSERA®

What should I tell my healthcare provider before taking VIREAD?

Tell your healthcare provider

- If you are pregnant or planning to become pregnant: The effects of VIREAD on pregnant women or their unborn babies are not known.
- If you are breast-feeding: Do not breast-feed if you are taking VIREAD. Do not breast-feed if you have HIV. If you are a woman who has or will have a baby, talk with your healthcare provider about the best way to feed your baby. If your baby does not already have HIV, there is a chance that the baby can get HIV through breast-feeding.
- If you have kidney or bone problems
- If you have liver problems including Hepatitis B Virus infection
- If you have HIV-1 Infection
- Tell your healthcare provider about all your medical conditions

TELL YOUR HEALTHCARE PROVIDER ABOUT ALL THE MEDICINES YOU TAKE, INCLUDING PRESCRIPTION AND NON-PRESCRIPTION MEDICINES AND DIETARY SUPPLEMENTS. ESPECIALLY TELL YOUR HEALTHCARE PROVIDER IF YOU TAKE:

- VIDEX, VIDEX EC (DIDANOSINE). VIREAD MAY INCREASE THE AMOUNT OF VIDEX IN YOUR BLOOD. YOU MAY NEED TO BE FOLLOWED MORE CAREFULLY IF YOU ARE TAKING VIDEX AND VIREAD TOGETHER. IF YOU ARE TAKING VIDEX AND VIREAD TOGETHER YOUR HEALTHCARE PROVIDER MAY NEED TO REDUCE YOUR DOSE OF VIDEX.
- REYATAZ (ATAZANAVIR SULFATE) OR KALETRA (LOPINAVIR/RITONAVIR). THESE MEDICINES MAY INCREASE THE AMOUNT OF VIREAD IN YOUR BLOOD, WHICH COULD RESULT IN MORE SIDE EFFECTS. YOU MAY NEED TO BE FOLLOWED MORE CAREFULLY IF YOU ARE TAKING VIREAD AND REYATAZ OR KALETRA TOGETHER. VIREAD MAY DECREASE THE AMOUNT OF REYATAZ IN YOUR BLOOD. IF YOU ARE TAKING VIREAD AND REYATAZ TOGETHER YOU SHOULD ALSO BE TAKING NORVIR (RITONAVIR).

IT IS A GOOD IDEA TO KEEP A COMPLETE LIST OF ALL THE MEDICINES THAT YOU TAKE. MAKE A NEW LIST WHEN MEDICINES ARE ADDED OR STOPPED. GIVE COPIES OF THIS LIST TO ALL OF YOUR HEALTHCARE PROVIDERS EVERY TIME YOU VISIT YOUR HEALTHCARE PROVIDER OR FILL A PRESCRIPTION.

How should I take VIREAD?

- Stay under a healthcare provider's care when taking VIREAD. Do not change your treatment or stop treatment without first talking with your healthcare provider.
- Take VIREAD exactly as your healthcare provider prescribed it. Follow the directions from your healthcare provider, exactly as written on the label. Set up a dosing schedule and follow it carefully.
- If you are taking VIREAD to treat your HIV or if you have HIV and HBV co-infection and are taking VIREAD, always take VIREAD in combination with other anti-HIV medicines. VIREAD and other products like VIREAD may be less likely to work in the future if you are not taking VIREAD with other anti-HIV medicines because you may develop resistance to those medicines.
- Talk to your doctor about taking an HIV test before you start treatment with VIREAD for chronic hepatitis B.
- The usual dose of VIREAD is 1 tablet once a day. If you have kidney problems, your healthcare provider may recommend that you take VIREAD less frequently.
- VIREAD may be taken with or without a meal.
- When your VIREAD supply starts to run low, get more from your healthcare provider or pharmacy. This is very important because the amount of virus in your blood may increase if the medicine is stopped for even a short time. The virus may develop resistance to VIREAD and become harder to treat.
- Only take medicine that has been prescribed specifically for you. Do not give VIREAD to others or take medicine prescribed for someone else.

What should I do if I miss a dose of VIREAD?

It is important that you do not miss any doses. If you miss a dose of VIREAD, take it as soon as possible and then take your next scheduled dose at its regular time. If it is almost time for your next dose, do not take the missed dose. Wait and take the next dose at the regular time. Do not double the next dose.

What happens if I take too much VIREAD?

If you suspect that you took more than the prescribed dose of VIREAD, contact your local poison control center or emergency room right away.

As with all medicines, VIREAD should be kept out of reach of children.

What should I avoid while taking VIREAD?

- Do not breast-feed. See "What should I tell my healthcare provider before taking VIREAD?"

What are the possible side effects of VIREAD?

- Clinical studies in patients with HIV-1: The most common side effects of VIREAD are: rash, headache, pain, diarrhea, depression, weakness, and nausea. Less common side effects include vomiting, dizziness, and intestinal gas.
  Clinical studies in patients with chronic hepatitis B: The most common side effect of VIREAD is nausea. Less common side effects include abdominal pain, diarrhea, headache, dizziness, fatigue, nasopharyngitis, back pain, and skin rash.
- Marketing experience: Other side effects reported since VIREAD has been marketed include: lactic acidosis, kidney problems (including decline or failure of kidney function), inflammation of the pancreas, inflammation of the liver, allergic reaction, shortness of breath, stomach pain, and high volume of urine and thirst caused by kidney problems. Muscle pain and muscle weakness, bone pain, and softening of the bone (which may contribute to fractures) as a consequence of kidney problems have been reported.
- Some patients treated with VIREAD have had kidney problems. If you have had kidney problems in the past or need to take another drug that can cause kidney problems, your healthcare provider may need to perform additional blood tests.
- Laboratory tests show changes in the bones of patients treated with VIREAD. If you have had bone problems in the past, your healthcare provider may need to perform additional tests or may suggest additional medication. Additionally, bone pain and softening of the bone (which may contribute to fractures) may occur as a consequence of kidney problems.
- Some patients taking antiviral drugs like VIREAD have developed a condition called lactic acidosis (a buildup in the blood of lactic acid, the same substance that causes your muscles to burn during heavy exercise). Symptoms of lactic acidosis include nausea, vomiting, unusual or unexpected stomach discomfort, and weakness. If you notice these symptoms or if your medical condition changes suddenly, call your healthcare provider right away.
- Changes in body fat have been seen in some patients taking anti-HIV-1 medicine. These changes may include increased amount of fat in the upper back and neck ("buffalo hump"), breast, and around the main part of your body (trunk). Loss of fat from the legs, arms and face may also happen. The cause and long term health effects of these conditions are not known at this time.
- In some patients with advanced HIV infection (AIDS), signs and symptoms of inflammation from previous infections may occur soon after anti-HIV treatment is started. It is believed that these symptoms are due to an improvement in the body's immune response, enabling the body to fight infections that may have been present with no obvious symptoms. If you notice any symptoms of infection, please inform your doctor immediately.
- If you have HBV infection or HIV and HBV infection together, you may have a "flare-up" of Hepatitis B, in which the disease suddenly returns in a worse way than before if you stop taking VIREAD. Do not stop taking VIREAD without your doctor's advice. After stopping VIREAD, tell your doctor immediately about any new, unusual, or worsening symptoms that you notice after stopping treatment. After you stop taking VIREAD, your doctor will still need to check your health and take blood tests to check your liver for several months.
- There have been other side effects in patients taking VIREAD. However, these side effects may have been due to other medicines that patients were taking or to the illness itself. Some of these side effects can be serious.
- This list of side effects is not complete. If you have questions about side effects, ask your healthcare provider. You should report any new or continuing symptoms to your healthcare provider right away. Your healthcare provider may be able to help you manage these side effects.

How do I store VIREAD?

- Keep VIREAD and all other medications out of reach of children.
- Store VIREAD at room temperature 77 °F (25 °C). It should remain stable until the expiration date printed on the label.
- Do not keep your medicine in places that are too hot or cold.
- Do not keep medicine that is out of date or that you no longer need. If you throw any medicines away make sure that children will not find them.

General advice about prescription medicines:

TALK TO YOUR HEALTHCARE PROVIDER IF YOU HAVE ANY QUESTIONS ABOUT THIS MEDICINE OR YOUR CONDITION. MEDICINES ARE SOMETIMES PRESCRIBED FOR PURPOSES OTHER THAN THOSE LISTED IN A PATIENT INFORMATION LEAFLET. IF YOU HAVE ANY CONCERNS ABOUT THIS MEDICINE, ASK YOUR HEALTHCARE PROVIDER. YOUR HEALTHCARE PROVIDER OR PHARMACIST CAN GIVE YOU INFORMATION ABOUT THIS MEDICINE THAT WAS WRITTEN FOR HEALTH CARE PROFESSIONALS. DO NOT USE THIS MEDICINE FOR A CONDITION FOR WHICH IT WAS NOT PRESCRIBED. DO NOT SHARE THIS MEDICINE WITH OTHER PEOPLE.

DO NOT USE IF SEAL OVER BOTTLE OPENING IS BROKEN OR MISSING.

What are the ingredients of VIREAD?

Active Ingredient: tenofovir disoproxil fumarate

Inactive Ingredients: croscarmellose sodium, lactose monohydrate, magnesium stearate, microcrystalline cellulose, and pregelatinized starch. The tablets are coated with Opadry II Y–30–10671–A, which contains FD&C blue #2 aluminum lake, hydroxypropyl methylcellulose 2910, lactose monohydrate, titanium dioxide, and triacetin.

VIREAD, EMTRIVA, HEPSERA and TRUVADA are registered trademarks of Gilead Sciences, Inc. ATRIPLA is a trademark of Bristol-Myers Squibb & Gilead Sciences, LLC. All other trademarks referenced herein are the property of their respective owners.

This Product was Repackaged By:

State of Florida DOH Central Pharmacy
104-2 Hamilton Park Drive
Tallahassee, FL 32304
United States

PRINCIPAL DISPLAY PANEL - Blister Pack Label

NDC 53808-0810-1

Viread®
(tenofovir disoproxil
fumarate) Tablets, 300 mg

30 tablets

Rx only